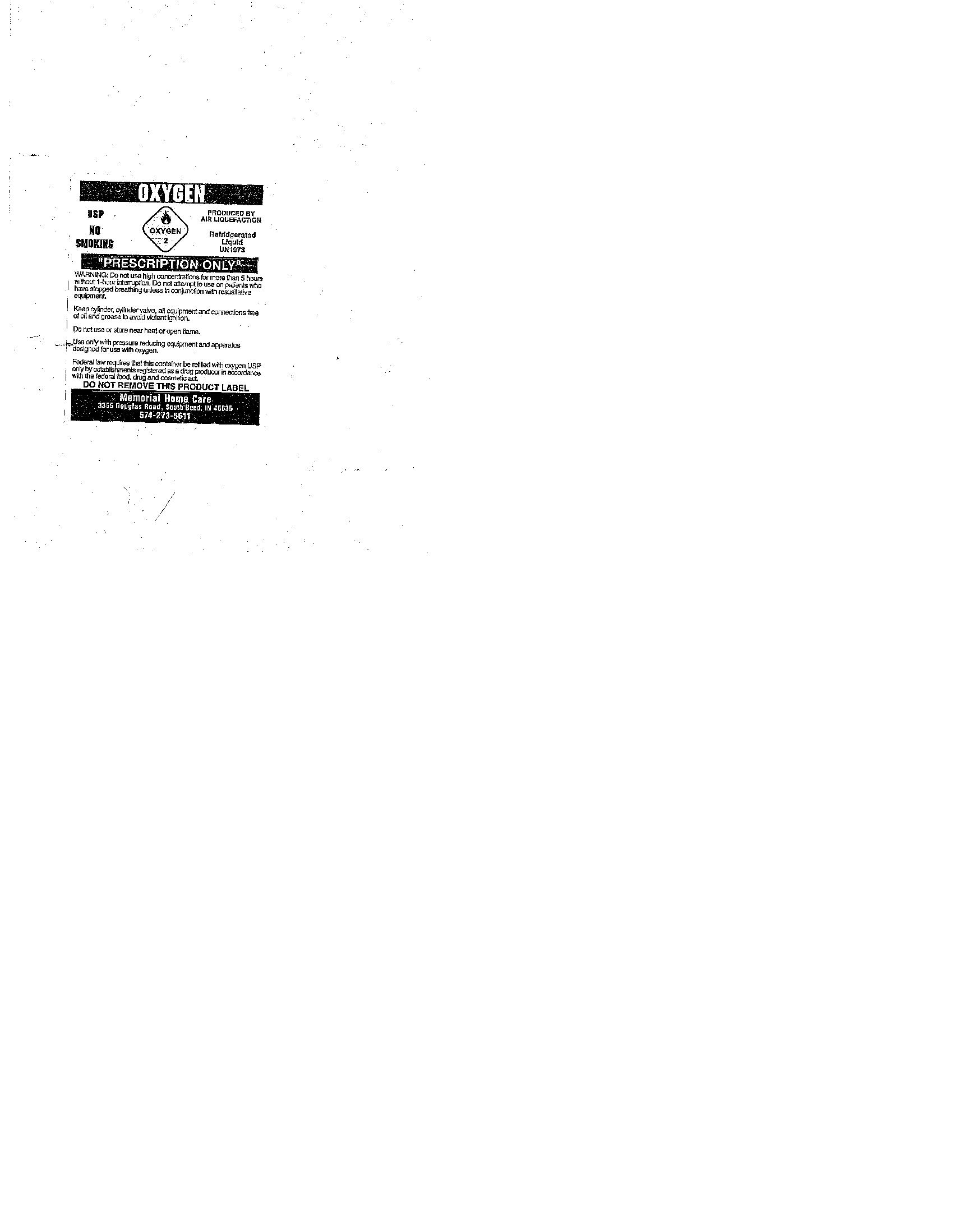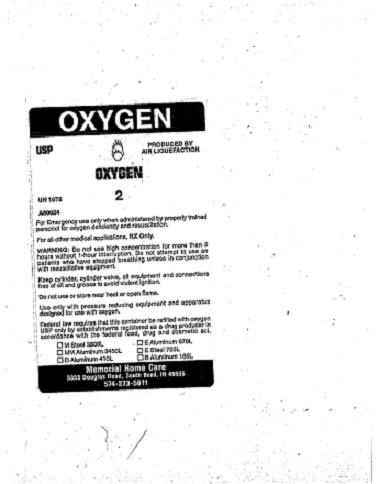 DRUG LABEL: oxygen
								
NDC: 58554-0002 | Form: GAS
Manufacturer: Memorial Home Care
Category: prescription | Type: HUMAN PRESCRIPTION DRUG LABEL
Date: 20100225

ACTIVE INGREDIENTS: oxygen 210 mL/1 L

PACKAGE LABEL

cylinder

PACKAGE LABEL

dewar